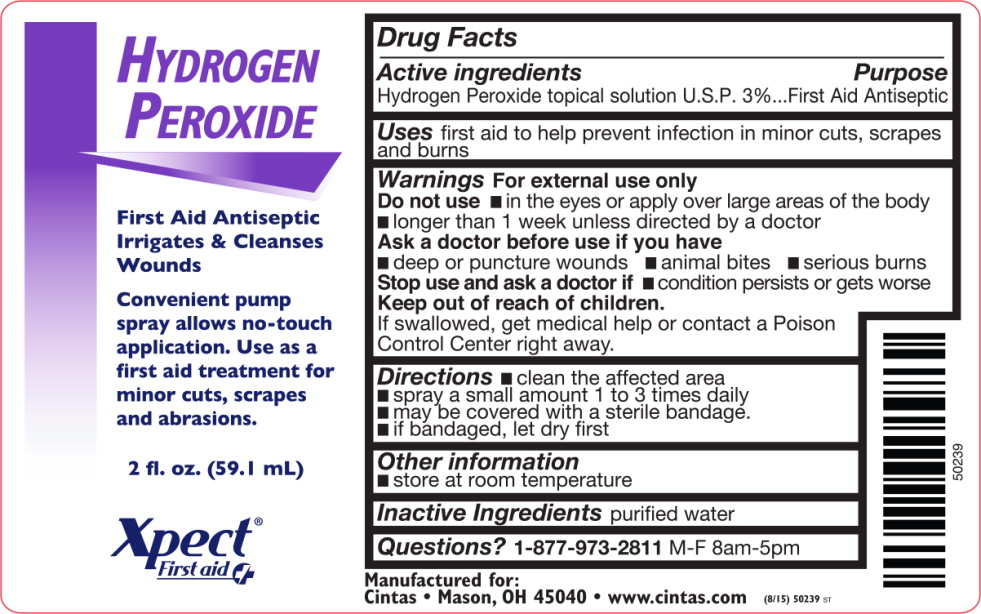 DRUG LABEL: Hydrogen Peroxide
NDC: 68421-5400 | Form: SPRAY
Manufacturer: Cintas First Aid & Safety
Category: otc | Type: HUMAN OTC DRUG LABEL
Date: 20150813

ACTIVE INGREDIENTS: hydrogen peroxide 43.275 g/1 L
INACTIVE INGREDIENTS: water

Drug Facts

Active Ingredients

Hydrogen Peroxide topical solution U.S.P. 3%

Purpose

First Aid Antiseptic

Uses

First aid to help prevent infection in minor cuts, scrapes & burns

Warnings For external use only

Do not use

- in eyes or apply over large areas of the body
- longer than one week unless directed by a doctor

Ask a doctor before use if you have

- deep or puncture wounds, animal bites, or serious burns

Stop use and ask a doctor if

- the condition persists or gets worse

Keep out of reach of children. If swallowed, get medical help or contact a Poison Control Center right away.

Directions

- clean the affected area
- spray a small amount of this product on the area 1 to 3 times daily
- may be covered with a sterile bandage
- if bandaged, let dry first

Other information

- store at room temperature

Inactive ingredients

purified water

Questions or Comments?

1-800-327-2704

Manufactured for: Respond Industries and
American First Aid, Mason, OH 45040
Rev. 04/13
#50225

PRINCIPAL DISPLAY PANEL – 2 oz. bottle label

Hydrogen
Peroxide

FIRST AID ANTISEPTIC

Convenient pump
spray allows no-touch
application. Use as a
first aid treatment
for minor cuts, scrapes
and abrasions

2 fl. oz. (59.1 mL)